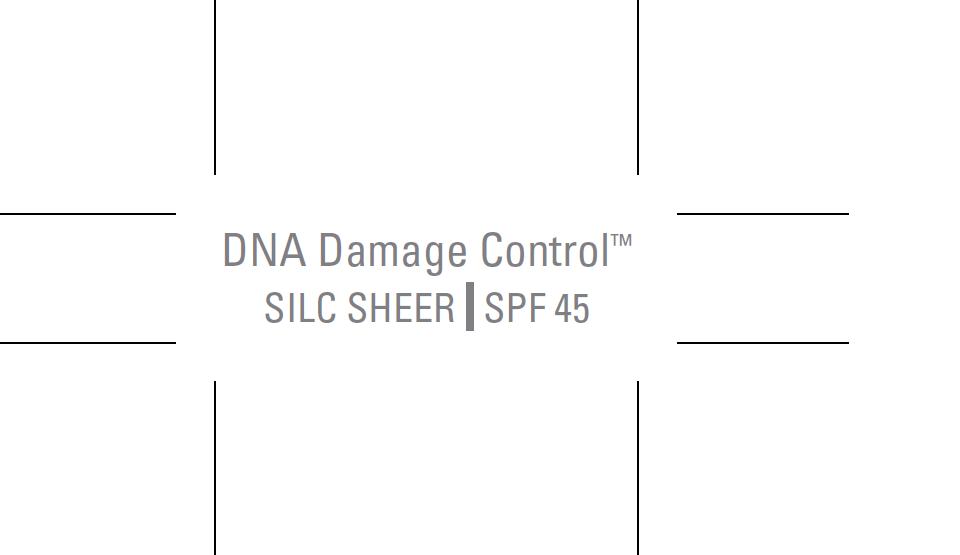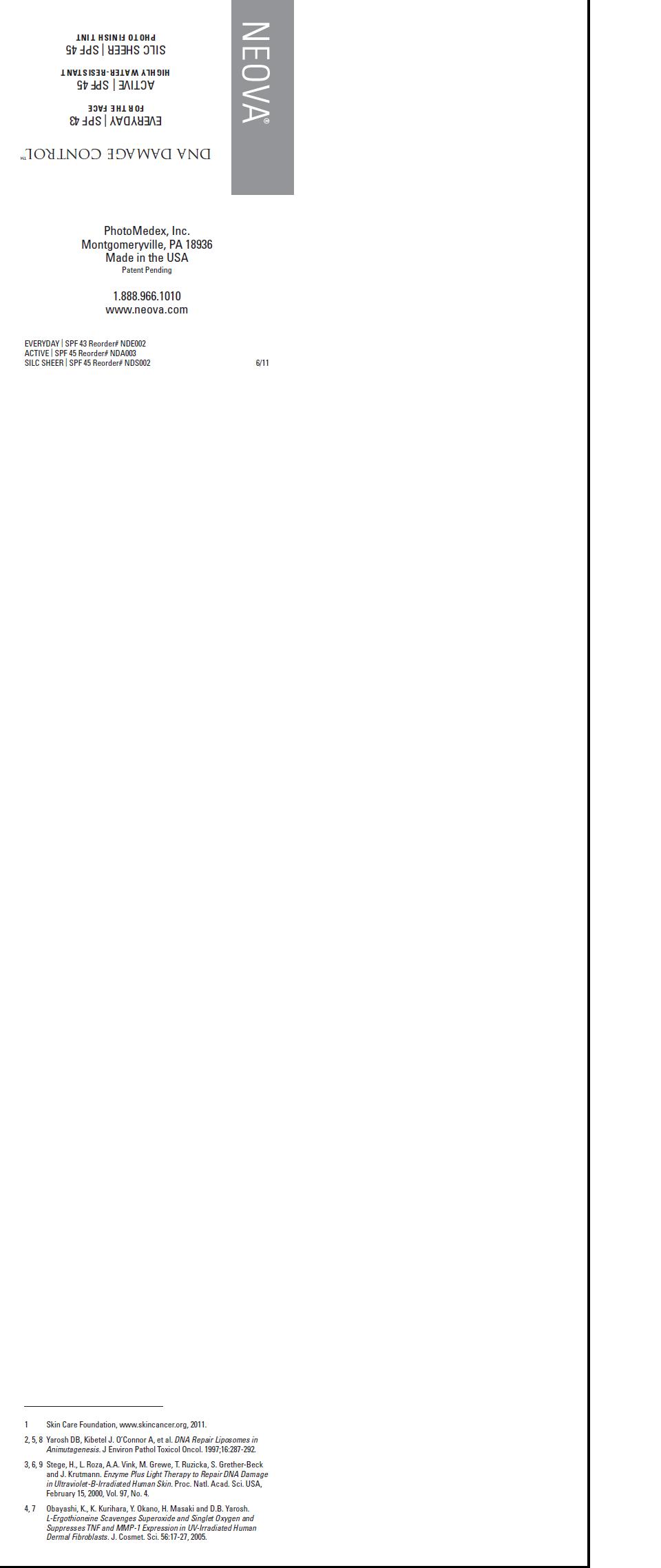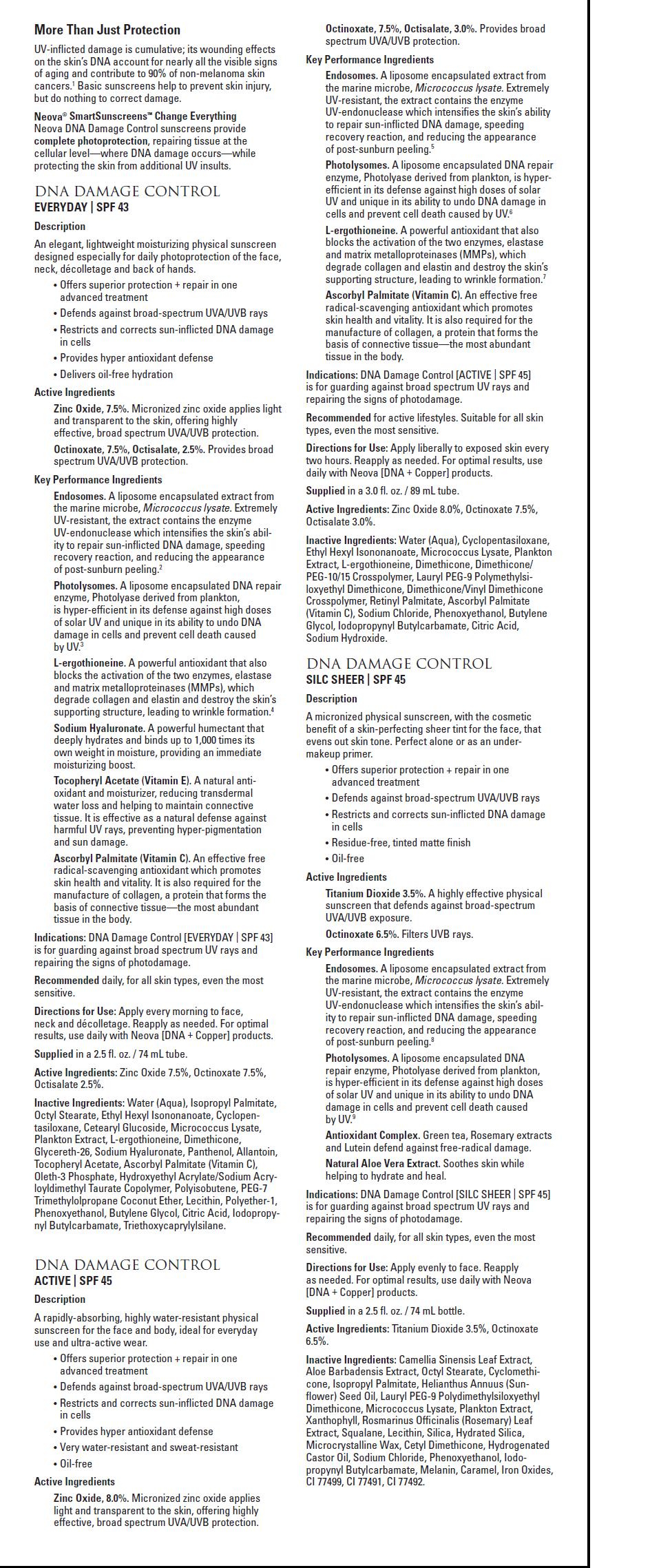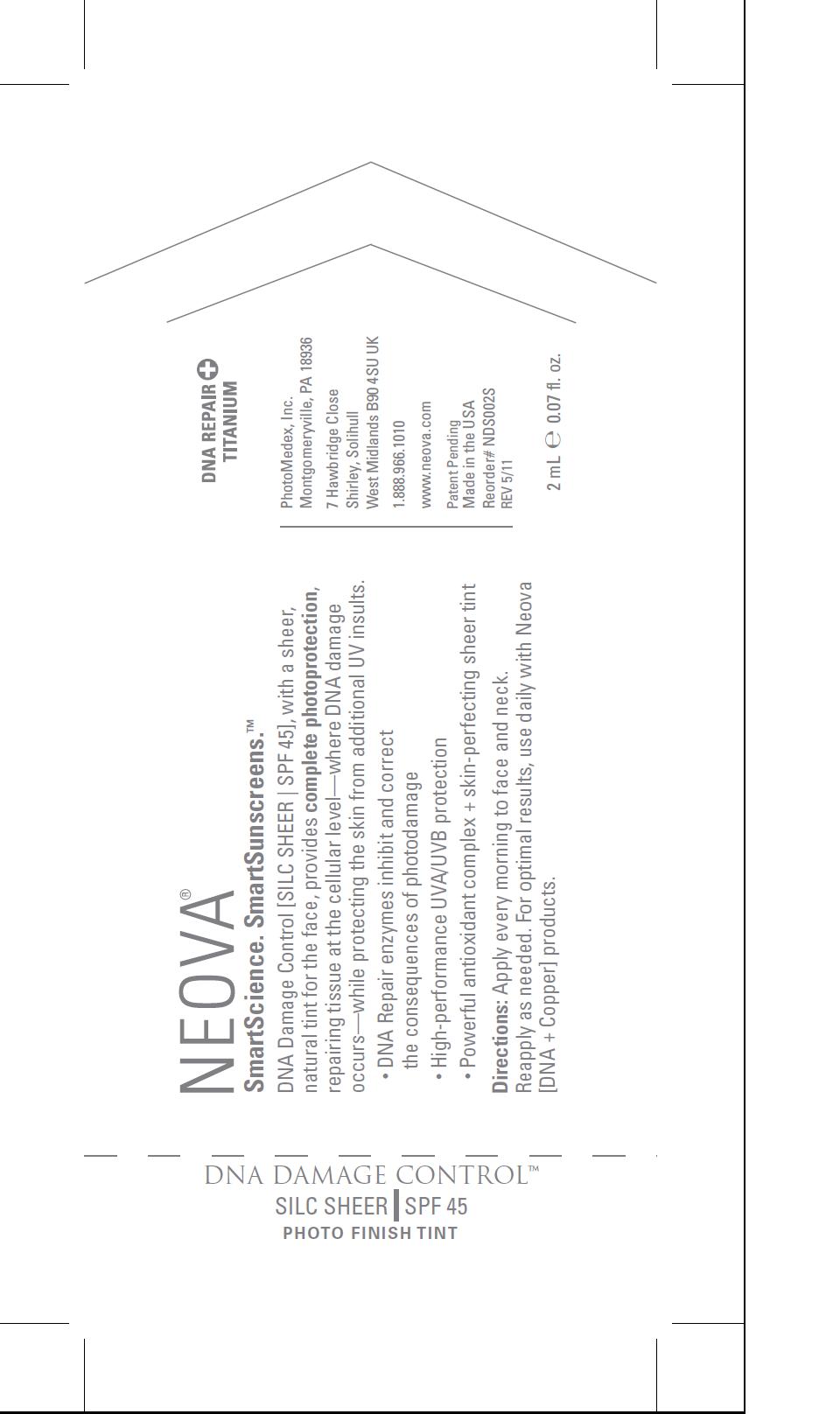 DRUG LABEL: Neova DNA Damage Control - Silc Sheer 
NDC: 62362-149 | Form: EMULSION
Manufacturer: PhotoMedex, Inc.
Category: otc | Type: HUMAN OTC DRUG LABEL
Date: 20120109

ACTIVE INGREDIENTS: Octinoxate 6.5 mL/100 mL; Titanium Dioxide 3.5 mL/100 mL
INACTIVE INGREDIENTS: Green Tea Leaf; Aloe Vera Leaf; Octyl Stearate; Cyclomethicone; Isopropyl Palmitate; Sunflower Oil; Lutein; Rosemary; Squalane; Egg Phospholipids; Silicon Dioxide; Hydrated Silica; Microcrystalline Wax; Hydrogenated Castor Oil; Sodium Chloride; Phenoxyethanol; Iodopropynyl Butylcarbamate; Caramel; Ferrosoferric Oxide; Ferric Oxide Red; Ferric Oxide Yellow

Neova DNA Damage Control - Silc Sheer SPF 45 - 2mL sample package insert

Directions for use:

Apply evenly to face. Reapply
as needed. For optimal results, use daily with Neova
[DNA + Copper] products.

Supplied

in a 2.5 fl. oz. / 74 mL bottle.

Active Ingredients:

Titanium Dioxide 3.5%, Octinoxate 6.5%.

Inactive Ingredients:

Camellia Sinensis Leaf Extract,
Aloe Barbadensis Extract, Octyl Stearate, Cyclomethicone,
Isopropyl Palmitate, Helianthus Annuus (Sunflower)
Seed Oil, Lauryl PEG-9 Polydimethylsiloxyethyl
Dimethicone, Micrococcus Lysate, Plankton Extract,
Xanthophyll, Rosmarinus Officinalis (Rosemary) Leaf
Extract, Squalane, Lecithin, Silica, Hydrated Silica,
Microcrystalline Wax, Cetyl Dimethicone, Hydrogenated
Castor Oil, Sodium Chloride, Phenoxyethanol, Iodopropynyl
Butylcarbamate, Melanin, Caramel, Iron Oxides,
CI 77499, CI 77491, CI 77492.

Image of package insert, package, and pouch

PkgInsertUniversalpg1.jpg PkgInsertUniversalpg2.jpg AmpuleSHEER.jpg PouchSHEER.jpg